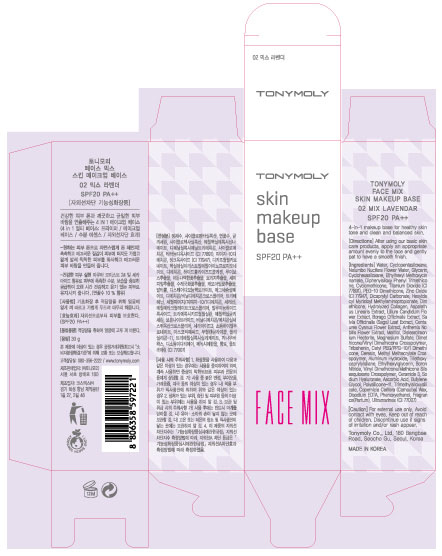 DRUG LABEL: TONYMOLY Face Mix Skin Makeup Base 02 Mix Lavendar SPF20
NDC: 59078-138 | Form: LOTION
Manufacturer: Tonymoly Co., Ltd.
Category: otc | Type: HUMAN OTC DRUG LABEL
Date: 20160201

ACTIVE INGREDIENTS: GLYCERIN 0.6 g/30 g; TITANIUM DIOXIDE 2.835 g/30 g; ZINC OXIDE 0.3 g/30 g; DIMETHICONE 0.3 g/30 g
INACTIVE INGREDIENTS: ULTRAMARINE BLUE; MAGNESIUM SULFATE; EDETATE DISODIUM; HYALURONATE SODIUM; DIMETHICONE/VINYL DIMETHICONE CROSSPOLYMER (SOFT PARTICLE); LILIUM CANDIDUM FLOWER; BORAGO OFFICINALIS WHOLE; CARNAUBA WAX; WATER; NELUMBO NUCIFERA FLOWER OIL; CYCLOMETHICONE 6; OCTINOXATE; DICAPRYLYL CARBONATE; DIPHENYLSILOXY PHENYL TRIMETHICONE; CYCLOMETHICONE; CETYL PEG/PPG-10/1 DIMETHICONE (HLB 2); CERESIN; CERAMIDE 3; ASPALATHUS LINEARIS WHOLE; CENTAUREA CYANUS FLOWER; CHAMAEMELUM NOBILE FLOWER; CYCLOMETHICONE 5; PHENOXYETHANOL; HEXYLDECYL MYRISTOYL METHYLAMINOPROPIONATE; MALTITOL; DISTEARDIMONIUM HECTORITE; DIMETHICONE/VINYL DIMETHICONE CROSSPOLYMER (HARD PARTICLE); TRIBEHENIN; ALUMINUM HYDROXIDE; ETHYLHEXYLGLYCERIN; BORON NITRIDE; ASCORBIC ACID; BUTYLENE GLYCOL

Active Ingredients

Dimethicone 1.00%, Ethylhexyl Methoxycinnamate 4.00%, Glycerin 2.00%, Titanium Dioxide 9.45%, Zinc Oxide 1.00%

Purpose

Skin Protectant

Use

SPF20 PA++

4-in-1 makeip base for healthy skin tone and clean and balanced skin.

Caution

For external use only. Avoid contact with eyes. Keep out of reach of children. Discontinue use if signs of irritation and/or rash appear.

Keep out of reach of children. Discontinue use if signs of irritation and/or rash appear.

Directions

After using our basic skin care products, apply an appropriate amount evenly to the face and gently pat to have an smooth finish.

Inactive Ingredients

Water, Cyclopentasiloxane, Nelumbo Nucifera Flower Water, Cyclohexasiloxane, Diphenylsiloxy Phenyl Trimethicone, Cyclomethicone, PEG10 Dimethicone, Dicaprylyl Carbonate, Hexyldecyl Myristoyl Methylaminopropionate, Maltitol, Disteardimonium Hectorite, Ultramarines (CI 77007), Magnesium Sulfate, Phenoxyethanol, Dimethicone/Vinyl Dimethicone Crosspolymer, Tribehenin, Cetyl PEG/PPG10/1 Dimethicone, Ceresin, Fragrance(Parfum), Triethoxycaprylylsilane, Methyl Methacrylate Crosspolymer, Aluminum Hydroxide, Ethylhexylglycerin, Disodium EDTA, Boron Nitride, Vinyl Dimethicone/Methicone Silsesquioxane Crosspolymer, Hydrolyzed Collagen, Ceramide 3, Sodium Hyaluronate, Ascorbic Acid, Butylene Glycol, Polysilicone11, Aspalathus Linearis Extract, Lilium Candidum Flower Extract, Borago Officinalis Extract, Salvia Officinalis (Sage) Leaf Extract, Centaurea Cyanus Flower Extract, Anthemis Nobilis Flower Extract, Trimethylsiloxysilicate, Copernicia Cerifera (Carnauba) Wax